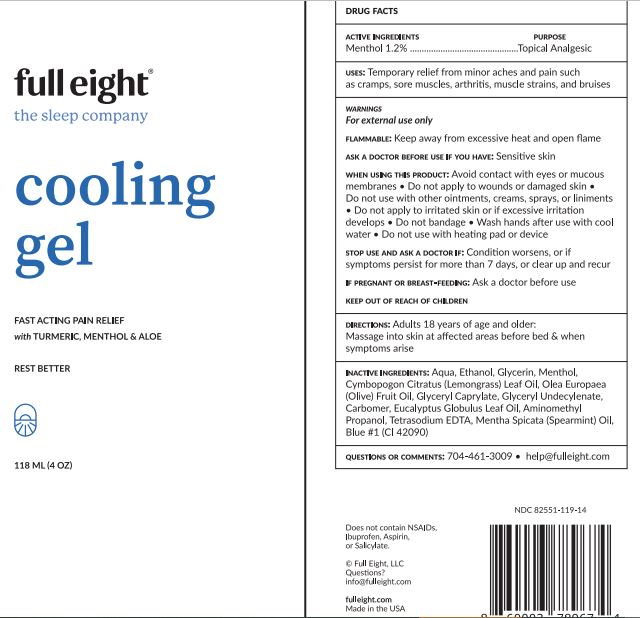 DRUG LABEL: COOLING
NDC: 82551-119 | Form: GEL
Manufacturer: FULL EIGHT Inc
Category: otc | Type: HUMAN OTC DRUG LABEL
Date: 20241011

ACTIVE INGREDIENTS: MENTHOL 1.2 g/100 mL
INACTIVE INGREDIENTS: CAMPHOR OIL; TROLAMINE; FD&C BLUE NO. 1; DMDM HYDANTOIN; WATER; ALCOHOL; CARBOMER HOMOPOLYMER, UNSPECIFIED TYPE; OLIVE OIL; EDETATE SODIUM TETRAHYDRATE; GLYCERIN; SPEARMINT OIL; EAST INDIAN LEMONGRASS OIL; EUCALYPTUS OIL; PEPPERMINT OIL

FULL EIGHT - COOLING GEL (82551-119)

ACTIVE INGREDIENT

MENTHOL 1.2%

PURPOSE

TOPICAL ANALGESIC

USE

Temporary relief from minor aches and pain such as cramps, sore muscles, arthritis, muscle strains, and bruises

WARNINGS

For external use only

Flammable: Keep away from excessive heat and open flame

Ask a doctor before use if you have: Sensitive skin

When using this product: Avoid contact with eyes or mucous membranes

- Do not apply to wounds or damaged skin
- Do not use with other ointments, creams, sprays, or liniments
- Do not apply to irritated skin or if excessive irritation develops
- Do not bandage
- Wash hands after use with cool water
- Do not use with heating pad or device

Stop use and ask a doctor if: Condition worsens, or if symptoms persist for more than 7 days, or clear up and recur

If pregnant or breast-feeding: Ask a doctor before use

KEEP OUT OF REACH OF CHILDREN.

DIRECTIONS

Adults 18 years of age and older: Massage into skin at affected areas before bed & when symptoms arise

INACTIVE INGREDIENTS

Purified water, Glycerin, SD Alcohol, Carbomer, Olive Oil, Tetrasodium EDTA, Spearmint Oil, Lemongrass oil, Eucalyptus Oil, Peppermint Oil, Camphor, Triethanolamine, F D & C Blue #1, DMDM Hydantoin

QUESTIONS OR COMMENTS?

704-461-3009 • help@fulleight.com